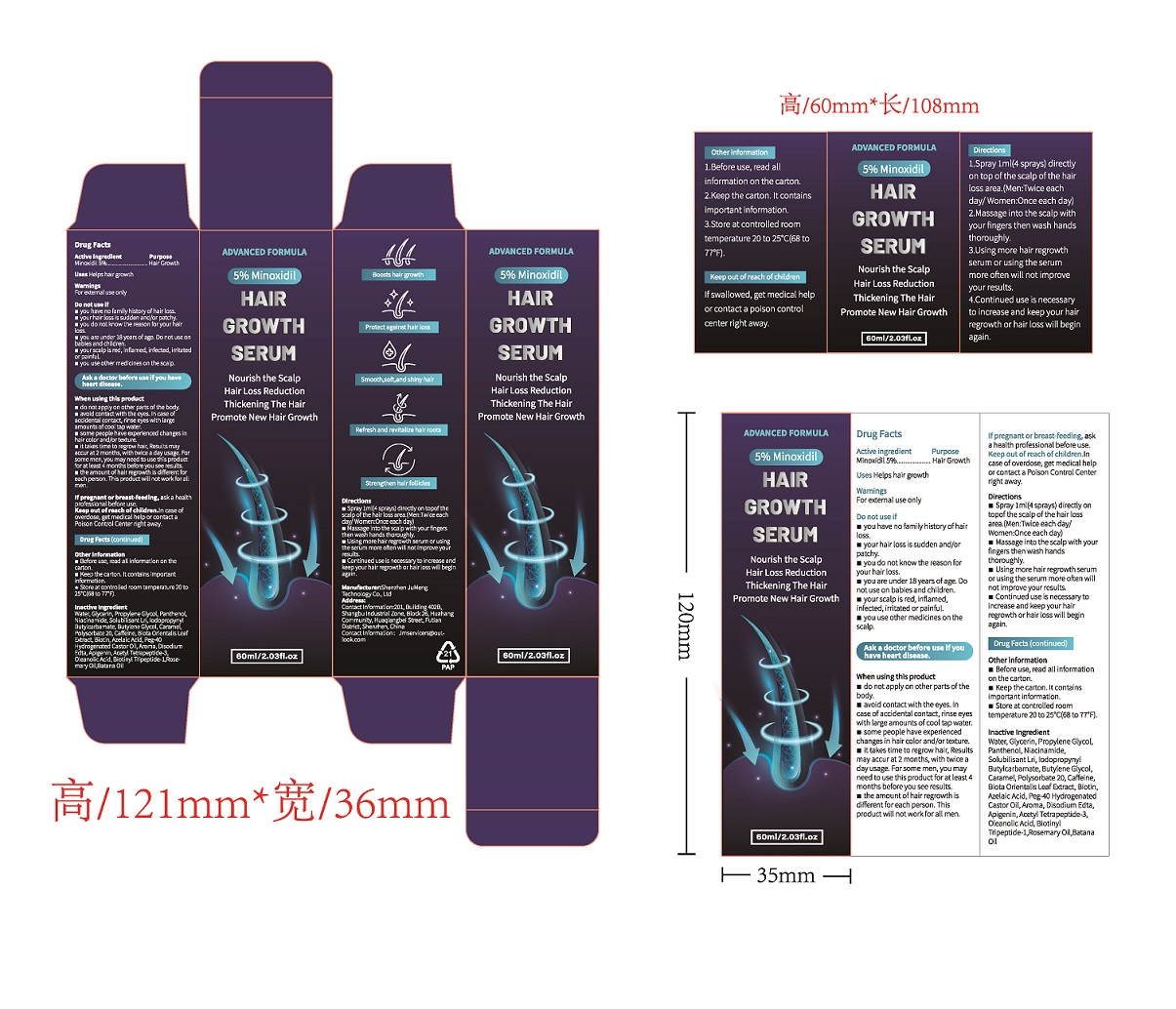 DRUG LABEL: Minoxidil Hair Growth Serum
NDC: 85092-001 | Form: LIQUID
Manufacturer: Shenzhen JuMeng Technology Co., Ltd
Category: otc | Type: HUMAN OTC DRUG LABEL
Date: 20250103

ACTIVE INGREDIENTS: MINOXIDIL 5 g/100 mL
INACTIVE INGREDIENTS: POLYSORBATE 20; PEG-40 HYDROGENATED CASTOR OIL; PLATYCLADUS ORIENTALIS LEAF; EDETATE DISODIUM; BIOTIN; NIACINAMIDE; WATER; PANTHENOL; AZELAIC ACID; APIGENIN; ACETYL TETRAPEPTIDE-3; OLEANOLIC ACID; ROSEMARY OIL; PPG-26-BUTETH-26; IODOPROPYNYL BUTYLCARBAMATE; CAFFEINE; BIOTINOYL TRIPEPTIDE-1; BUTYLENE GLYCOL; PROPYLENE GLYCOL; CARAMEL; ELAEIS OLEIFERA SEED OIL; GLYCERIN

85092-001

Active ingredient

Minoxidil 5%

Purpose

Hair Growth

Uses

Helps hair growth

Warnings

For external use only

Do not use if

● you have no family history of hair loss.
● your hair loss is sudden and/or patchy.

● you do not know the reason for your hair loss.
● you are under 18 years of age. Do not use on babies and children.
● your scalp is red, inflamed, infected, irritated or painful
● you use other medicines on the scalp.

When using this product

● do not apply on other parts of the body.
● avoid contact with the eyes. In case of accidental contact, rinse eyes with large amounts of cool tap water.
● some people have experienced changes in hair color and/or texture.
● it takes time to regrow hair, Results may accur at 2 months, with twice a day usage. For some men, you may need to use this product for at least 4 months before you see results.
● the amount of hair regrowth is different for each person. This product will not work for all men.

If pregnant or breast-feeding

ask a health professional before use.

Keep out of reach of children.

In case of overdose, get medical help or contact a Poison Control Center right away.

Directions

● Spray 1ml(4 sprays) directly on topof the scalp of the hair loss area.(Men:Twice each day/ Women:Once each day)
● Massage into the scalp with your fingers then wash hands thoroughly.
● Using more hair regrowth serum or using the serum more often will not improve your results.
● Continued use is necessary to increase and keep your hair regrowth or hair loss will begin again.

Other information

• Before use, read all information on carton
• Keep the carton. It contains important information.
• Store at controlled room temperature 20° to 25° C (68° to 77° F)

Inactive Ingredient

Water, Glycerin, Propylene Glycol, Panthenol, Niacinamide, Solubilisant Lri, Iodopropynyl Butylcarbamate, Butylene Glycol, Caramel, Polysorbate 20, Caffeine, Biota Orientalis Leaf Extract, Biotin, Azelaic Acid, Peg-40 Hydrogenated Castor Oil, Aroma, Disodium Edta, Apigenin, Acetyl Tetrapeptide-3, Oleanolic Acid, Biotinyl Tripeptide-1,Rosemary Oil,Batana Oil